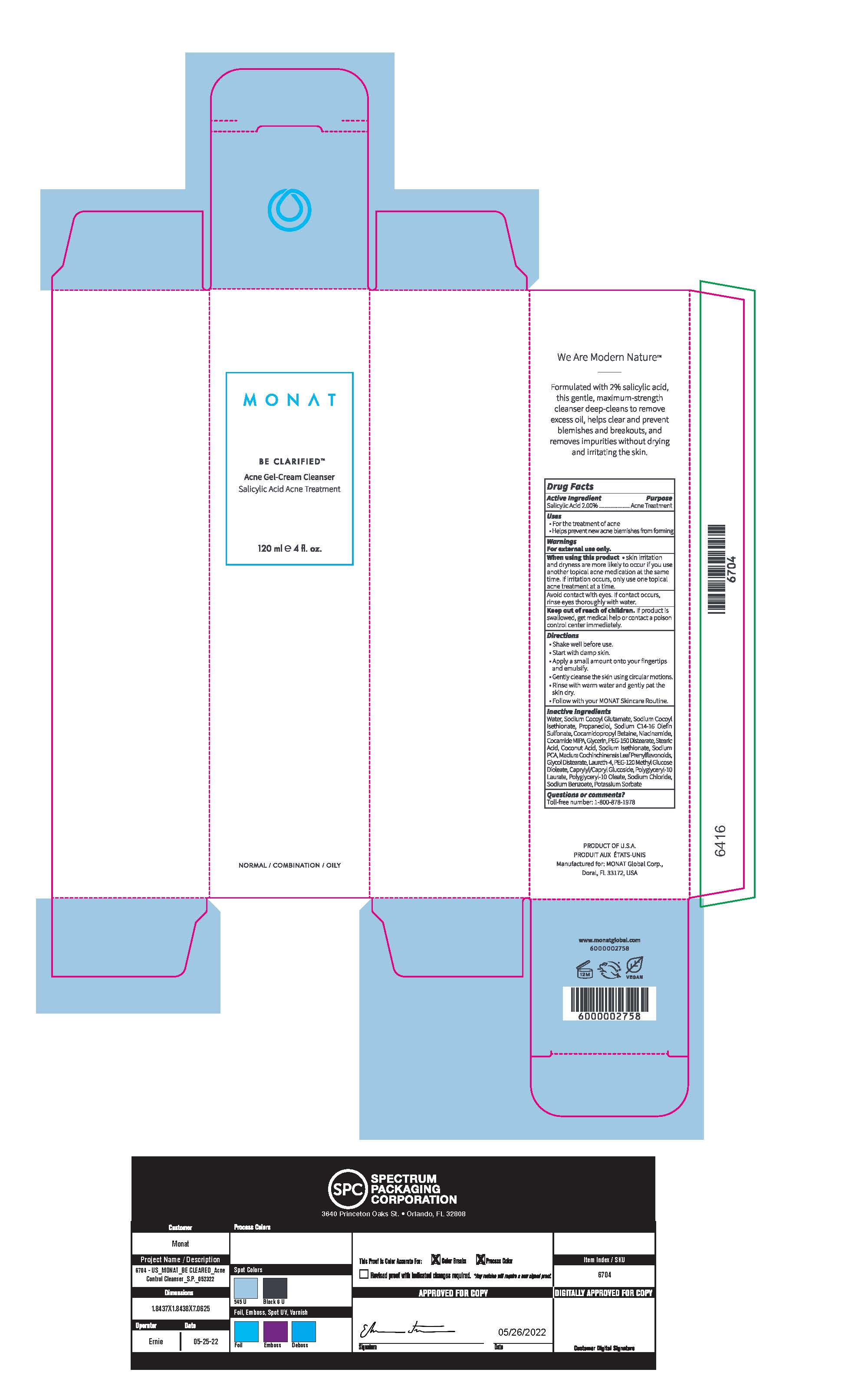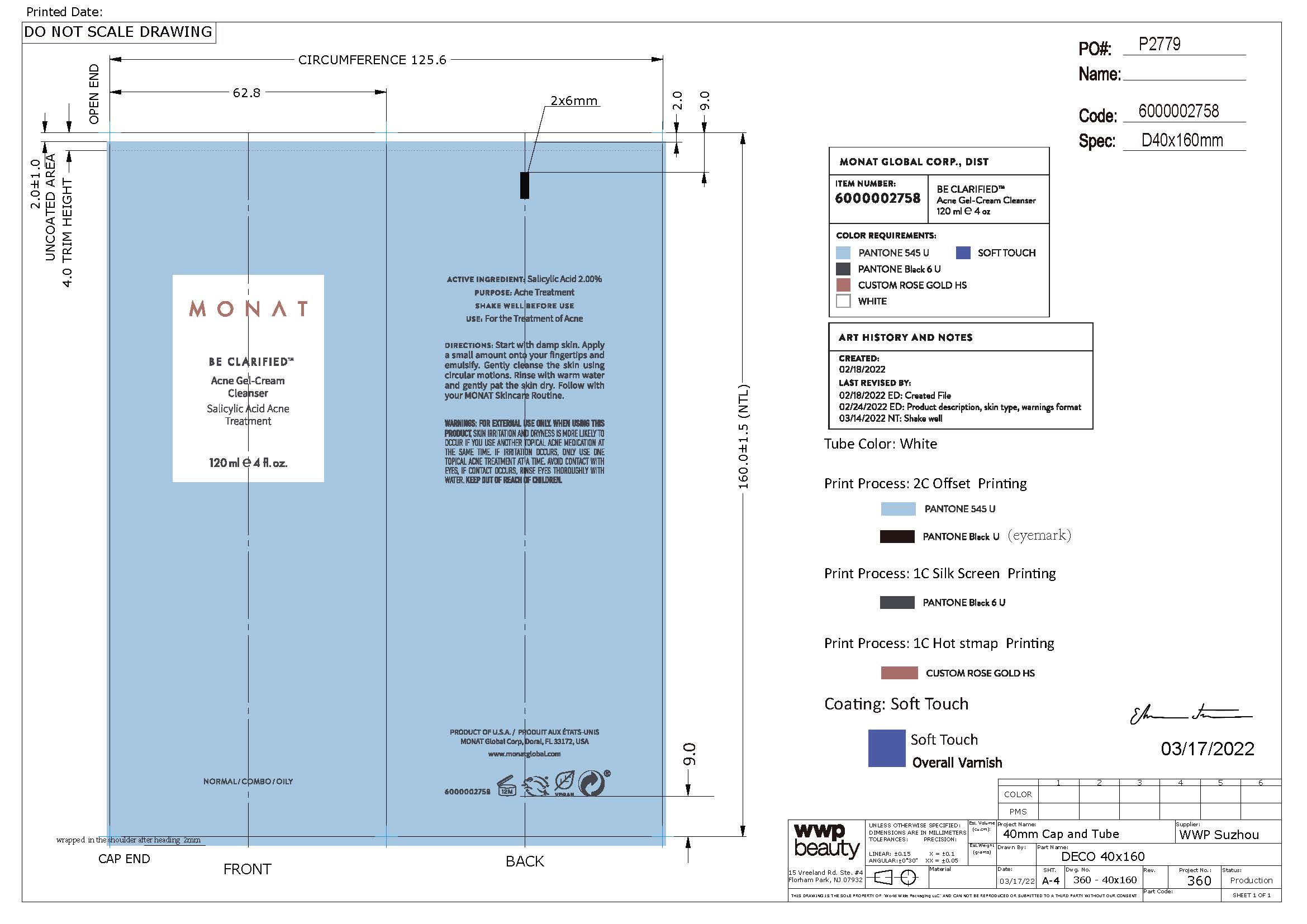 DRUG LABEL: Liquid
NDC: 61354-091 | Form: LIQUID
Manufacturer: Oxygen Development LLC
Category: otc | Type: HUMAN OTC DRUG LABEL
Date: 20230322

ACTIVE INGREDIENTS: SALICYLIC ACID 2 mg/100 mg
INACTIVE INGREDIENTS: SODIUM COCOYL GLUTAMATE 4.2 mg/100 mg; PROPANEDIOL 2.99 mg/100 mg; SODIUM C14-16 OLEFIN SULFONATE 2 mg/100 mg; COCO MONOISOPROPANOLAMIDE 0.56 mg/100 mg; COCAMIDOPROPYL BETAINE 1.79 mg/100 mg; SODIUM COCOYL ISETHIONATE 1.68 mg/100 mg; WATER 78.25 mg/100 mg; PEG-120 METHYL GLUCOSE DIOLEATE 1.087 mg/100 mg; SODIUM PYRROLIDONE CARBOXYLATE 0.5 mg/100 mg

BE CLARIFIED Acne Gel-Cream Cleanser Salicylic Acid Acne treatment

Active Ingredient

Salicylic Acid

Purpose

Acne Treatment

Uses

For the treatment of acne

Helps prevent new acne blemishes from forming

Warnings

For external use only

When using this product

Skin irritation and dryness are more likely to occur if you use another topical acne medication at the same time. If irritation occurs, only use one topical acne treatment at a time.

Avoid contact with eyes. If products occurs, rinse eyes thoroughly with water

Keep out of reach of children

If product is swallowed, get medical help or contact a poison control center immediately

Directions

Shake well before use

Start with damp skin

Apply a small amount onto your fingertips and emulsify

Gently cleanse the skin using circular motions

Rinse with warm water and gently pat the skin dry

Follow with your MONAT Skincare Routine

Inactive Ingredients

Water/Aqua, Sodium Cocoyl Glutamate, Sodium Cocoyl Isethionate, Propanediol, Sodium C14-16 Olefin Sulfonate, Cocamidopropyl Betaine, Niacinamide, Cocamide MIPA, Glycerin, PEG-150 Distearate, Stearic Acid, Coconut Acid, Sodium PCA, Maclura Cochinchinensis Leaf Prenylflavonoids, Glycol Distearate, Laureth-4, PEG-120 Methyl Glucose Dioleate, Caprylyl/Capryl Glucoside, Polyglyceryl-10 Laurate, Polyglyceryl-10 Oleate, Sodium Chloride, SOdium Benzoate, Potassium Sorbate